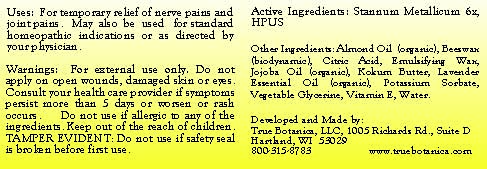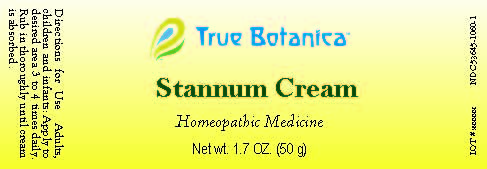 DRUG LABEL: Stannum Metallicum
NDC: 53645-1060 | Form: CREAM
Manufacturer: True Botanica, LLC
Category: homeopathic | Type: HUMAN OTC DRUG LABEL
Date: 20250114

ACTIVE INGREDIENTS: TIN 6 [hp_X]/50 mL
INACTIVE INGREDIENTS: ALMOND OIL; YELLOW WAX; CITRIC ACID MONOHYDRATE; GLYCERIN; JOJOBA OIL; GARCINIA INDICA SEED BUTTER; LAVENDER OIL; CETOSTEARYL ALCOHOL; POLYSORBATE 60; POTASSIUM SORBATE; .ALPHA.-TOCOPHEROL; WATER

Stannum Cream

ACTIVE INGREDIENT

Stannum Metallicum 6X, HPUS

PURPOSE

Enter section text here

Uses:

For temporary relief of nerve pain and joint pains. May also be used for standard homeopathic indications or as directed by your physician.

Warnings:

For external use only. Do not apply on open wounds, damaged skin or eyes. Consult your health care provider if symptoms persist more than 5 days or worsen or rash occurs. Do not use if allergic to any of the ingredients.

Keep out of the reach of children.

DO NOT USE

TAMPER EVIDENT: Do not use if safety seal is broken before first use.

Directions for Use:

Adults, children and infants: Apply to desired area 3-4 times daily. Rub in thoroughly until cream is absorbed.

Other Ingredients:

Almond Oil, Beeswax, Citric Acid, Emulsifying Wax, Jojoba Oil, Kokum Butter, Lavender Essential Oil, Potassium Sorbate, Vegetable Glycerine, Vitamin E, Water.

QUESTIONS

Developed and Made by

True Botanica, LLC

1005 Richards Rd., Suite D

Hartland, WI 53029

800-315-8783

www.truebotanica.com